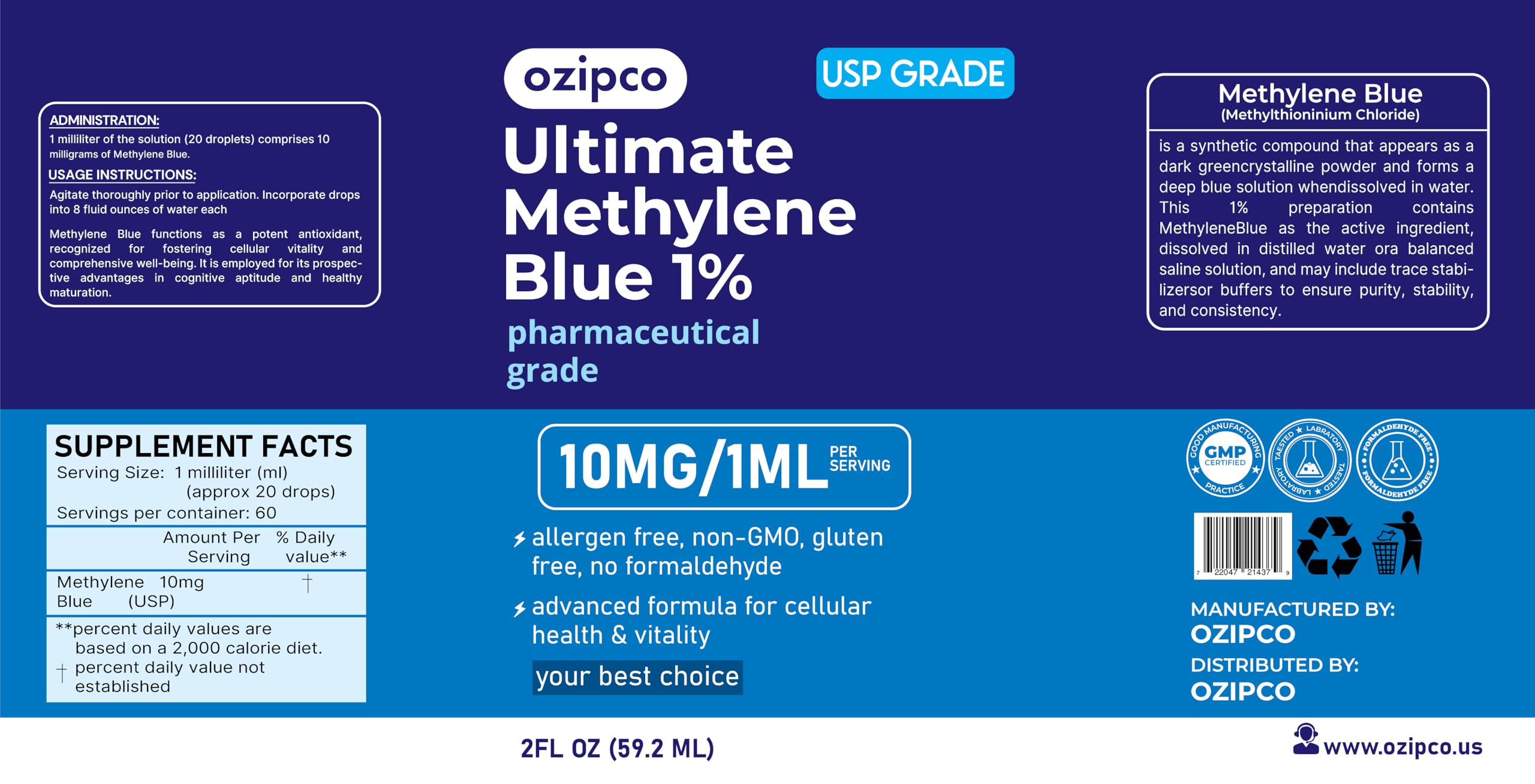 DRUG LABEL: Ozipco 1% METHYLENE BLUE
NDC: 86241-003 | Form: SOLUTION
Manufacturer: Fast Sold LLC
Category: otc | Type: HUMAN OTC DRUG LABEL
Date: 20260121

ACTIVE INGREDIENTS: METHYLENE BLUE 1 g/100 mL
INACTIVE INGREDIENTS: AQUA 99 mL/100 mL

DOSAGE AND ADMINISTRATION

NET: 2 FL.OZ (59.2 ml)

DIRECTIONS

Mix 1 ml (20 drops) of the solution with 200 ml of water, or use according to your established research protocols.

PURPOSE

Memory consolidation

Oxidative stress defense
Mental fatigue resistance
Manage BMS Symptoms Effectively

INACTIVE INGREDIENT

Pure Deionizer Water

Keep out of the reach of children.

WARNINGS

1. Consult a health care professional before using the product orally or on the skin.

2. This product is for adult use only.

3. Keep out of the reach of children.

4. Natural residue may occur. Shake well before use.

5. The product is a strong dye. Avoid contact with clothing and surfaces.

6. "STORAGE Store in a dry cool place away from direct sunlight."

7. This statement has not been evaluated by the food and drug administration. This product is a dietary supplement. This product is not intended to diagnose, cure or prevent any disease.